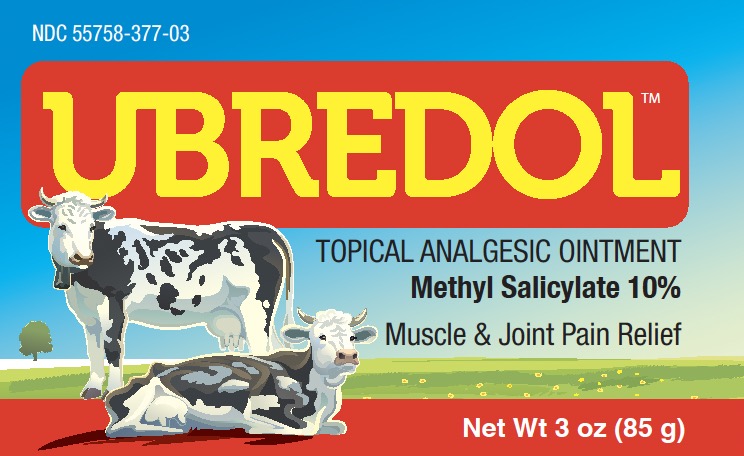 DRUG LABEL: Ubredol
NDC: 55758-377 | Form: OINTMENT
Manufacturer: Pharmadel LLC
Category: otc | Type: HUMAN OTC DRUG LABEL
Date: 20251204

ACTIVE INGREDIENTS: METHYL SALICYLATE 10 g/100 g
INACTIVE INGREDIENTS: CAMPHOR, (-)-; LEVOMENTHOL; D&C YELLOW NO. 11; MINERAL OIL; PARAFFIN; PROPYLPARABEN; PETROLATUM; LANOLIN OIL

Ubredol Methyl Salicylate 10% (WP)(DA)

Active ingredient & Purpose

Active ingredient | Purpose
Methyl salicylate 10% .................. | Topical analgesic

Uses

For the temporary relief of minor aches and pains of muscles and joints associated with:

- simple backache
- arthritis
- strains
- bruises
- sprains

Warnings

For external use only. Avoid contact with the eyes.

Do not

- apply on wounds or irritated skin
- bandage tightly

Stop use and ask doctor immediately if

- condition worsens
- symptoms persist for more than 7 days or clear up and occur again within a few days

If pregnant or breast-feeding,

ask a health care professional before use.

Keep out of reach of children.

If swallowed get medical help, or contact a Poison Control Center immediately.

Directions

- adults and children 12 years of age and older: apply to affected area not more than 3 to 4 times daily
- children under 12 years of age: do not use, consult a doctor

Other information

- store between 59°- 86°F (15 - 30°C)
- do not use if clear seal over jar is broken, torn or missing

Inactive ingredients

camphor, D&C yellow #11, eucalyptus oil, lanolin oil, levomenthol, mineral oil, petrolatum, propylparaben, tea tree oil

Distributed by:

Pharmadel LLC

New Castle, DE 19720

+1-866-359-3478